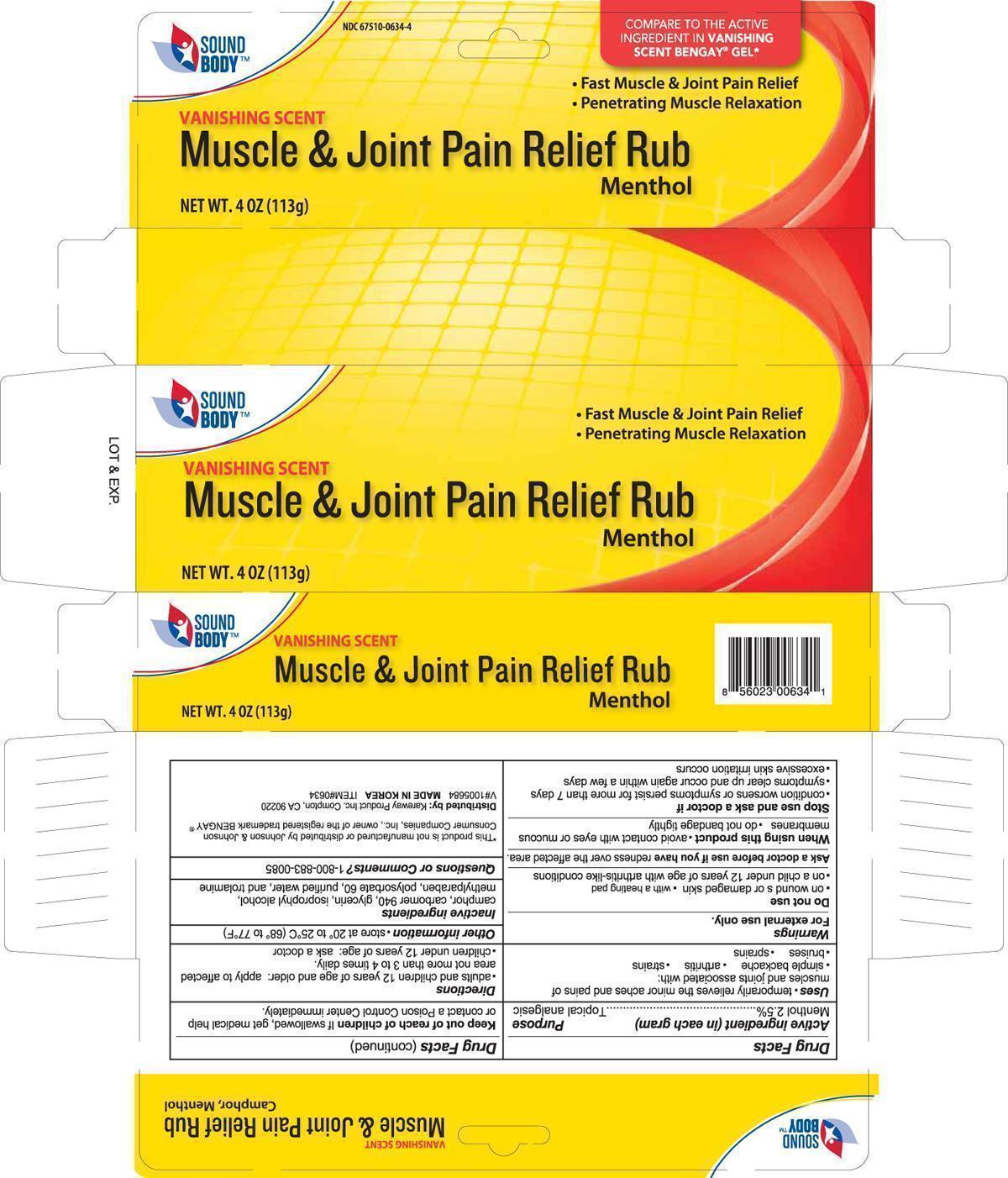 DRUG LABEL: Muscle and Joint
NDC: 67510-0634 | Form: GEL
Manufacturer: Kareway Product, Inc.
Category: otc | Type: HUMAN OTC DRUG LABEL
Date: 20221117

ACTIVE INGREDIENTS: MENTHOL 2.5 g/100 g
INACTIVE INGREDIENTS: CAMPHOR (SYNTHETIC); CARBOMER HOMOPOLYMER TYPE C; GLYCERIN; ISOPROPYL ALCOHOL; METHYLPARABEN; POLYSORBATE 60; WATER; TROLAMINE

Sound Body Muscle and Joint Rub

Active ingredient

Menthol 2.5%

purpose

Topical analgesic

Uses

temporarily relieves the minor aches and pains of muscles and joints associated with:

- simple backache
- arthritis
- strains
- bruises
- sprains

Warnings

For external use only

Do not use

- on wound s or damaged skin
- with a heating pad
- on a child under 12 years of age with arthritis-like conditions

Ask a doctor before use if you have

redness over the affected area.

When using this product

- avoid contact with eyes or mucous membranes
- do not bandage tightly

Stop use and ask a doctor if

- condition worsens or symptoms persist for more than 7 days
- symptoms clear up and occur again within a few days
- excessive skin irritation occurs

Keep out of reach of children

If swallowed, get medical help or contact a Poison Control Center immediately.

Directions

- adults and children 12 years of age and older: apply to affected area not more than 3 to 4 times daily
- children under 12 years of age: ask a doctor

Other information

- store at 20° to 25°C (68° to 77°F)

Inactive ingredients

camphor, carbomer 940, glycerin, isoprophyl alcohol, methylparaben, polysorbate 60, purified water, and trolamine

Questions or Comments?

1-800-833-0085

Package label

Muscle and joint pain relief rub